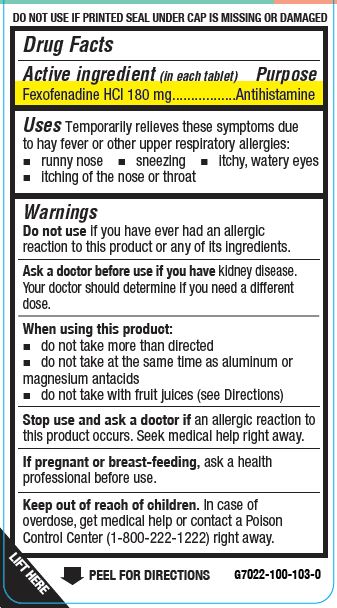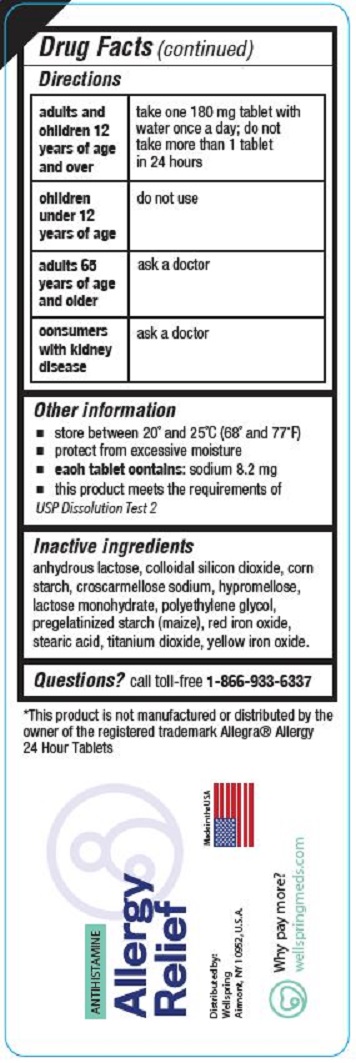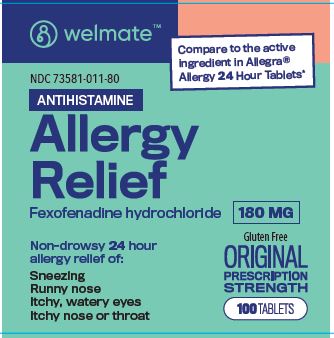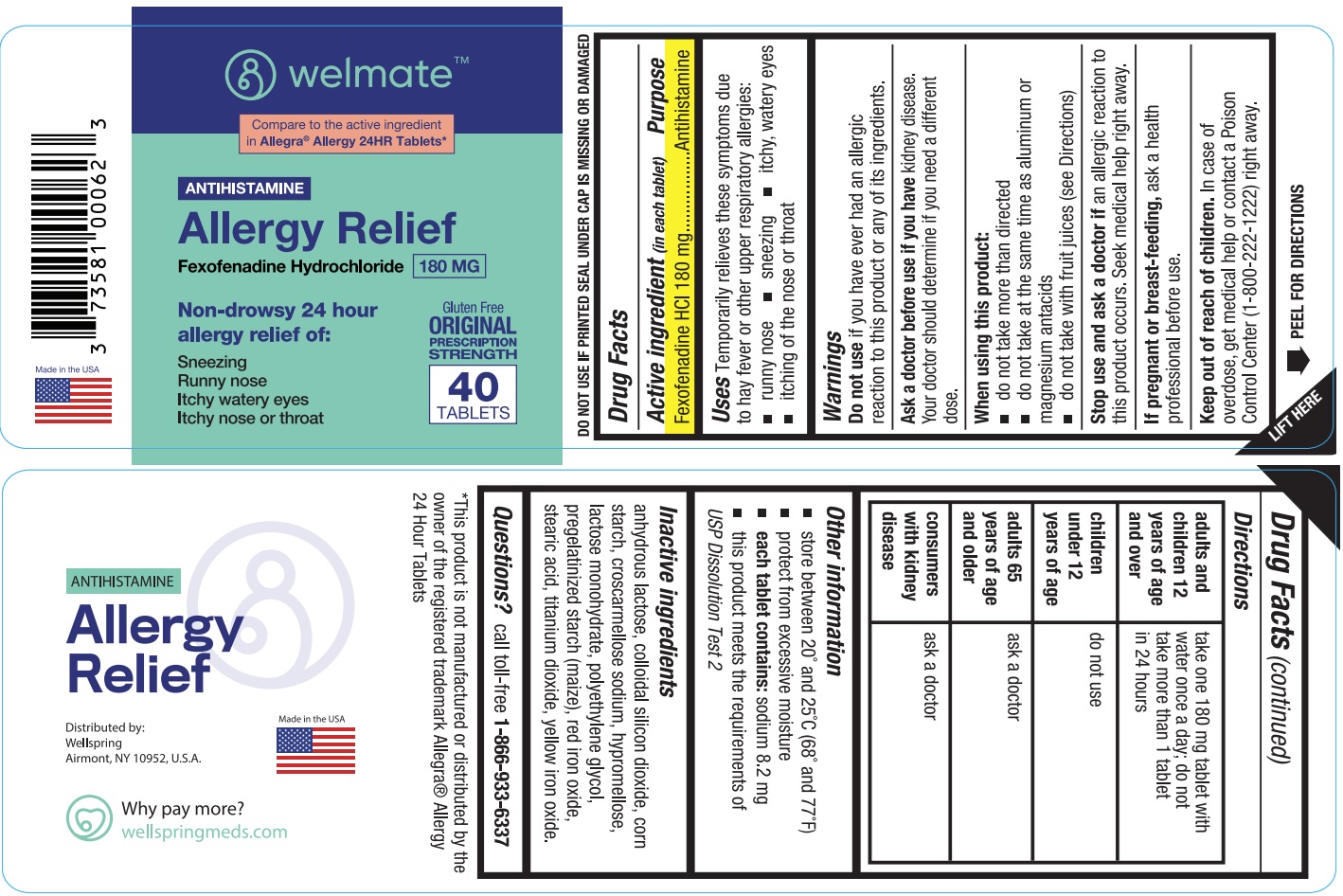 DRUG LABEL: ALLERGY RELIEF
NDC: 73581-011 | Form: TABLET
Manufacturer: YYBA CORP
Category: otc | Type: HUMAN OTC DRUG LABEL
Date: 20251127

ACTIVE INGREDIENTS: FEXOFENADINE HYDROCHLORIDE 180 mg/1 1
INACTIVE INGREDIENTS: ANHYDROUS LACTOSE; SILICON DIOXIDE; STARCH, CORN; CROSCARMELLOSE SODIUM; HYPROMELLOSE, UNSPECIFIED; LACTOSE MONOHYDRATE; POLYETHYLENE GLYCOL, UNSPECIFIED; CORN; FERRIC OXIDE RED; STEARIC ACID; TITANIUM DIOXIDE; FERRIC OXIDE YELLOW

YYBA (as PLD) - WELMATE ANTIHISTAMINE ALLERGY RELIEF (73581-011)

Active ingredient (in each tablet)

Fexofenadine HCl 180 mg

Purpose

Antihistamine

Uses

Temporarily relieves these symptoms due to hay fever or other upper respiratory allergies:

- runny nose
- sneezing
- itchy, watery eyes
- itching of the nose or throat

Warnings

Do not use if you have ever had an allergic reaction to this product or any of its ingredients.

Ask a doctor before use if you have kidney disease. Your doctor should determine if you need a different dose.

When using this product:

- do not take more than directed
- do not take at the same time as aluminum or magnesium antacids
- do not take with fruit juices (see Directions)

Stop use and ask a doctor if an allergic reaction to this product occurs. Seek medical help right away.

If pregnant or breast-feeding, ask a health professional before use.

Keep out of reach of children. In case of overdose, get medical help or contact a Poison Control Center (1-800-222-1222) right away.

Directions

adults and children 12 years of age and over | take one 180 mg tablet with water once a day; do not take more than 1 tablets in 24 hours
children under 12 years of age | do not use
adults 65 years and older | ask a doctor
consumers with kidney disease | ask a doctor

Other information

- store between 20° and 25°C (68° and 77°F)
- protect from excessive moisture
- each tablet contains:sodium 8.2 mg
- this product meets the requirements of USP Dissolution Test 2

Inactive ingredients

anhydrous lactose, colloidal silicon dioxide, corn starch, croscarmellose sodium, hypromellose, lactose monohydrate, polyethylene glycol, pregelatinized starch (maize), red iron oxide, stearic acid, titanium dioxide, yellow iron oxide.

Questions?

call toll-free 1-800-935-6737